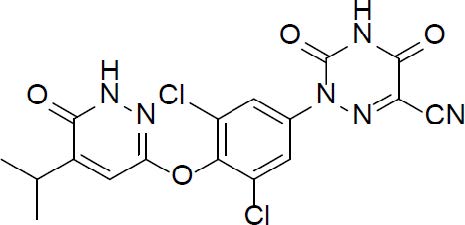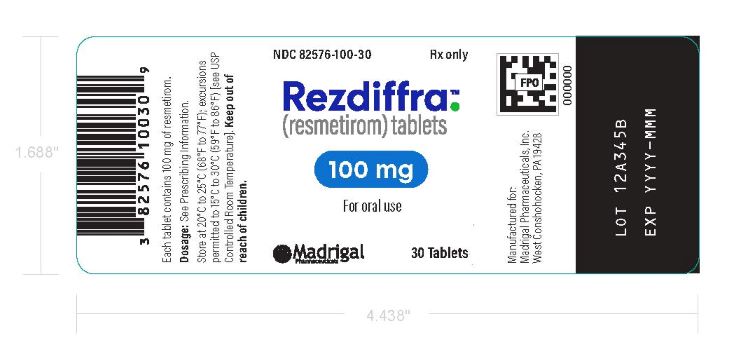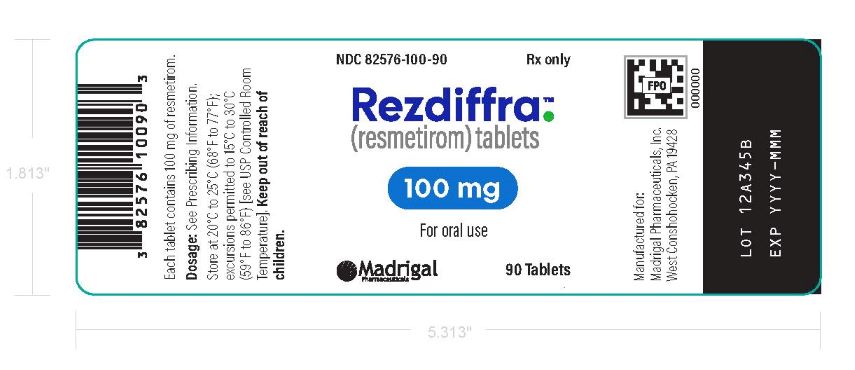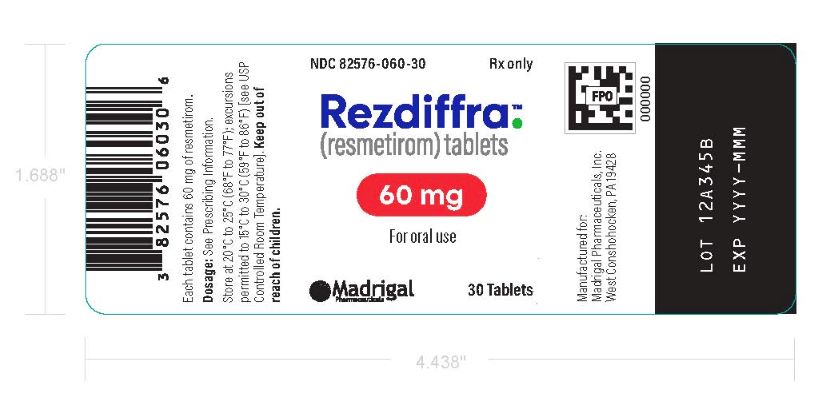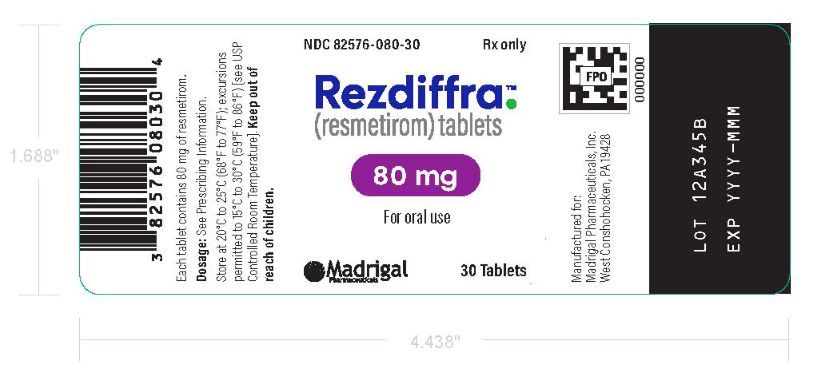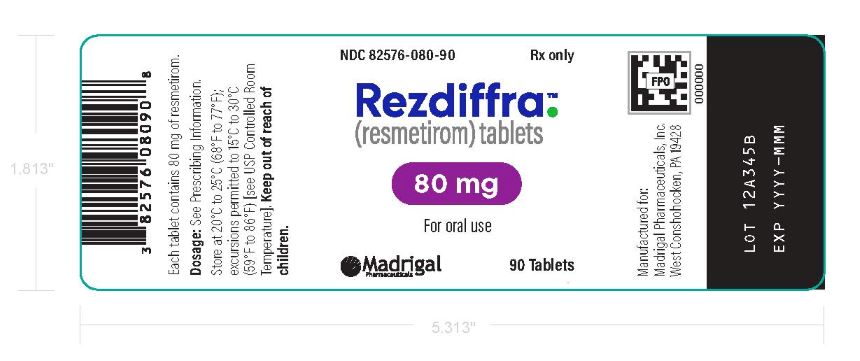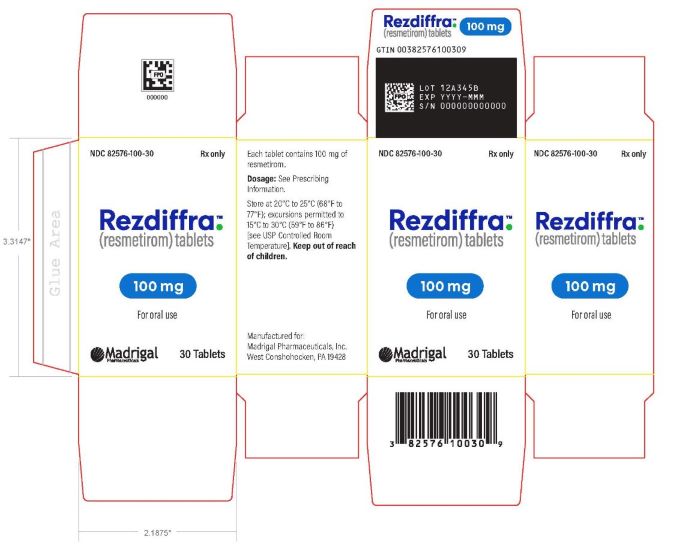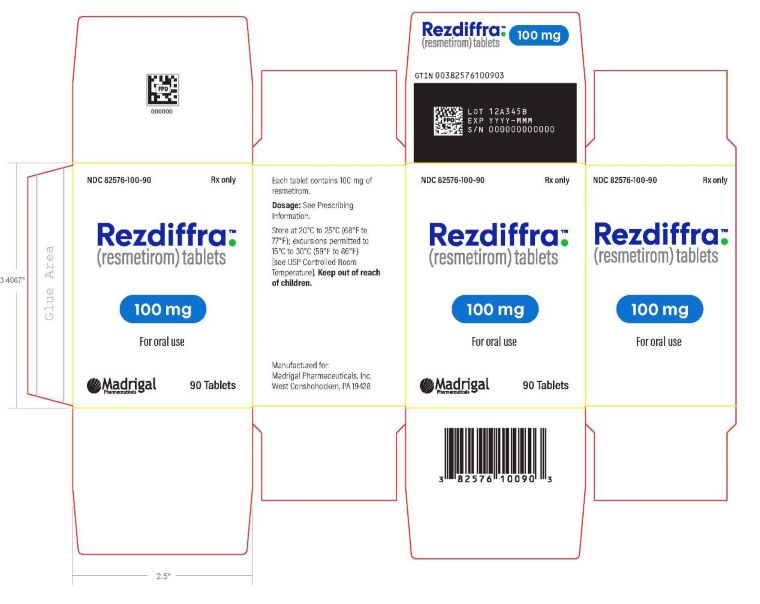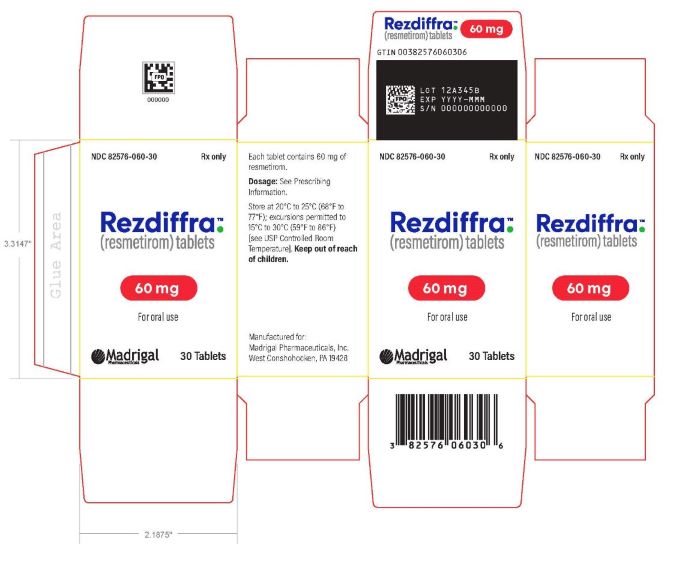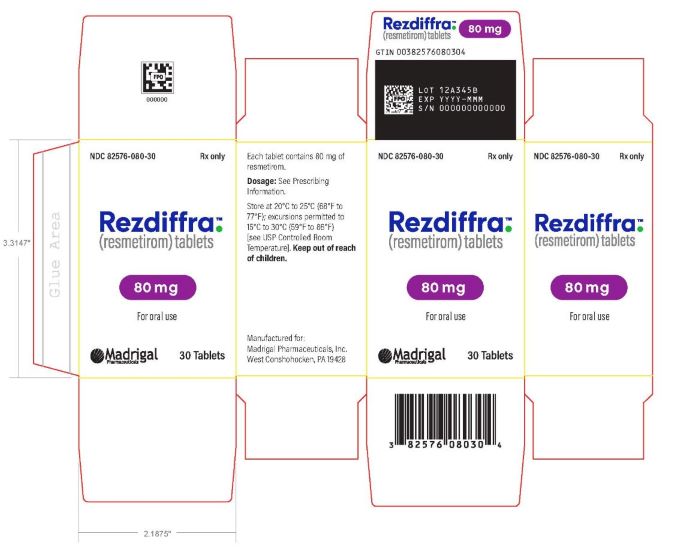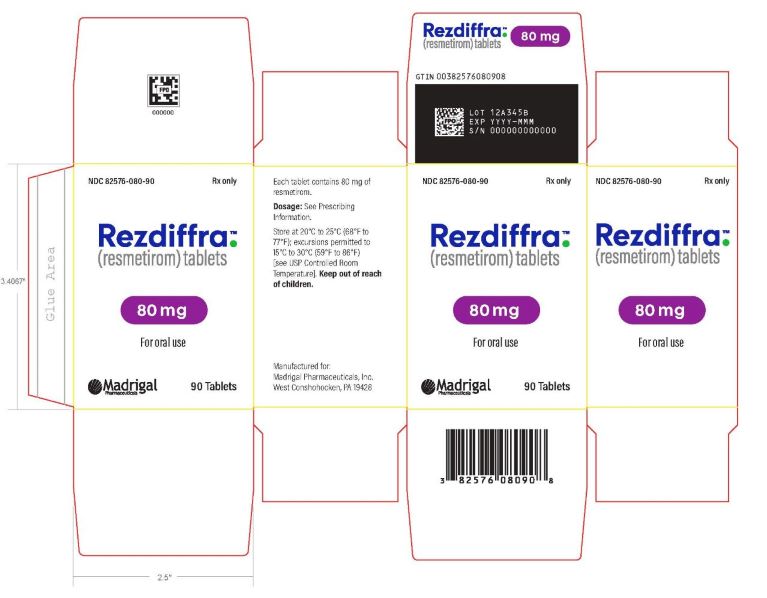 DRUG LABEL: REZDIFFRA
NDC: 82576-060 | Form: TABLET, COATED
Manufacturer: Madrigal Pharmaceuticals, Inc.
Category: prescription | Type: HUMAN PRESCRIPTION DRUG LABEL
Date: 20251222

ACTIVE INGREDIENTS: RESMETIROM 60 mg/1 1

HIGHLIGHTS OF PRESCRIBING INFORMATION

These highlights do not include all the information needed to use REZDIFFRA safely and effectively. See full prescribing information for REZDIFFRA.
REZDIFFRA (resmetirom) tablets, for oral use
Initial U.S. Approval: 2024

RECENT MAJOR CHANGES

Dosage and Administration (2.1) 12/2025

1 INDICATIONS AND USAGE

REZDIFFRA is a thyroid hormone receptor-beta (THR-beta) agonist indicated in conjunction with diet and exercise for the treatment of adults with noncirrhotic nonalcoholic steatohepatitis (NASH) with moderate to advanced liver fibrosis (consistent with stages F2 to F3 fibrosis).

This indication is approved under accelerated approval based on improvement of NASH and fibrosis. Continued approval for this indication may be contingent upon verification and description of clinical benefit in confirmatory trials. (1)

Limitations of Use

Avoid use of REZDIFFRA in patients with decompensated cirrhosis. (1)

2 DOSAGE AND ADMINISTRATION

- The recommended dosage of REZDIFFRA is based on actual body weight. For patients weighing:

o <100 kg, the recommended dosage is 80 mg orally once daily.

o ≥100 kg, the recommended dosage is 100 mg orally once daily.

Administer REZDIFFRA with or without food. Swallow REZDIFFRA tablets whole; do not split, crush, or chew tablets (2.1)

- See full prescribing information for REZDIFFRA dosage modifications with concomitant use of moderate CYP2C8 inhibitors. (2.2)

3 DOSAGE FORMS AND STRENGTHS

Tablets: 60 mg, 80 mg, and 100 mg (3)

4 CONTRAINDICATIONS

None.

5 WARNINGS AND PRECAUTIONS

- Hepatotoxicity: Monitor patients during treatment with REZDIFFRA for elevations in liver tests and for the development of liver-related adverse reactions. Discontinue REZDIFFRA and continue to monitor the patient if hepatotoxicity is suspected. (5.1)
- Gallbladder-Related Adverse Reactions: Cholelithiasis and cholecystitis were observed more often in REZDIFFRA-treated patients. If cholelithiasis is suspected, gallbladder diagnostic studies and appropriate clinical follow-up are indicated. If an acute gallbladder event such as acute cholecystitis is suspected, interrupt REZDIFFRA treatment until the event is resolved. (5.2)

6 ADVERSE REACTIONS

The most common adverse reactions with REZDIFFRA (reported in at least 5% of patients and higher compared to placebo) are: diarrhea, nausea, pruritus, vomiting, constipation, abdominal pain, and dizziness. (6.1)

To report SUSPECTED ADVERSE REACTIONS, contact Madrigal Pharmaceuticals, Inc. at 1-800-905-0324 or FDA at 1-800-FDA-1088 or www.fda.gov/medwatch.

7 DRUG INTERACTIONS

- Strong or Moderate CYP2C8 Inhibitors: Concomitant use not recommended (strong inhibitor [e.g., gemfibrozil]); or reduce REZDIFFRA dosage (moderate inhibitor [e.g., clopidogrel]). (2.2, 7.1)
- Atorvastatin, Pravastatin, Rosuvastatin and Simvastatin: Limit the daily dosage of the statin as recommended. (5.3, 7.2)
- CYP2C8 Substrates: Monitor patients more frequently for substrate- related adverse reactions. (7.2)

8 USE IN SPECIFIC POPULATIONS

Hepatic Impairment: Avoid use of REZDIFFRA in patients with moderate to severe hepatic impairment (Child-Pugh Class B or C). (8.7)

FULL PRESCRIBING INFORMATION

1 INDICATIONS AND USAGE

REZDIFFRA is indicated in conjunction with diet and exercise for the treatment of adults with noncirrhotic nonalcoholic steatohepatitis (NASH) with moderate to advanced liver fibrosis (consistent with stages F2 to F3 fibrosis).

This indication is approved under accelerated approval based on improvement of NASH and fibrosis [see Clinical Studies (14)]. Continued approval for this indication may be contingent upon verification and description of clinical benefit in confirmatory trials.

Limitations of Use

Avoid use of REZDIFFRA in patients with decompensated cirrhosis [see Use in Specific Populations (8.7), Clinical Pharmacology (12.3)].

2 DOSAGE AND ADMINISTRATION

2.1 Recommended Dosage and Administration

The recommended dosage of REZDIFFRA is based on actual body weight. For patients weighing:

- <100 kg, the recommended dosage is 80 mg orally once daily.
- ≥100 kg, the recommended dosage is 100 mg orally once daily.

Administer REZDIFFRA with or without food [see Clinical Pharmacology (12.3)].

Swallow REZDIFFRA tablets whole; do not split, crush, or chew tablets.

Advise patients that if a dose is missed, do not take the missed dose and resume with the next scheduled dose.

2.2 Dosage Modifications for CYP2C8 Inhibitors

Concomitant use of REZDIFFRA with strong CYP2C8 inhibitors (e.g., gemfibrozil) is not recommended [see Drug Interactions (7.1)].

If REZDIFFRA is used concomitantly with a moderate CYP2C8 inhibitor (e.g., clopidogrel) [see Drug Interactions (7.1)], reduce the dosage of REZDIFFRA:

- <100 kg, reduce the dosage of REZDIFFRA to 60 mg once daily.
- ≥100 kg, reduce the dosage of REZDIFFRA to 80 mg once daily.

3 DOSAGE FORMS AND STRENGTHS

REZDIFFRA Tablets:

- 60 mg: white oval-shaped film-coated tablets debossed with “P60” on one side and plain on the other side.
- 80 mg: yellow, oval-shaped, film-coated tablets debossed with “P80” on one side and plain on the other side.
- 100 mg: beige to pink, oval-shaped, film-coated tablets debossed with “P100” on one side and plain on the other side.

4 CONTRAINDICATIONS

None.

5 WARNINGS AND PRECAUTIONS

5.1 Hepatotoxicity

Hepatotoxicity has been observed with use of REZDIFFRA. One patient had normal alanine aminotransferase (ALT), aspartate aminotransferase (AST), and total bilirubin (TB) levels at baseline, who received REZDIFFRA 80 mg daily, developed substantial elevations of liver biochemistries that resolved when treatment was interrupted. After reinitiating REZDIFFRA, the patient had elevations of ALT, AST, and TB. Peak values observed were 58 x upper limit of normal (ULN) for ALT, 66 x ULN for AST, 15 x ULN for TB, with no elevation of alkaline phosphatase (ALP). Elevations in liver enzymes were accompanied by elevations in immunoglobulin G levels, suggesting drug-induced autoimmune-like hepatitis (DI-ALH). The liver tests returned to baseline following hospitalization and discontinuation of REZDIFFRA without any therapeutic intervention.

Monitor patients during treatment with REZDIFFRA for elevations in liver tests and for the development of liver-related adverse reactions. Monitor for symptoms and signs of hepatotoxicity (e.g., fatigue, nausea, vomiting, right upper quadrant pain or tenderness, jaundice, fever, rash, and/or eosinophilia [>5%]). If hepatotoxicity is suspected, discontinue REZDIFFRA and continue to monitor the patient. If laboratory values return to baseline, weigh the potential risks against the benefits of restarting REZDIFFRA. If laboratory values do not return to baseline, consider DI-ALH or autoimmune liver disease in the evaluation of elevations in liver tests.

5.2 Gallbladder-Related Adverse Reactions

In clinical trials, cholelithiasis, acute cholecystitis, and obstructive pancreatitis (gallstone) were observed more often in REZDIFFRA-treated patients than in placebo-treated patients. If cholelithiasis is suspected, gallbladder diagnostic studies and appropriate clinical follow-up are indicated. If an acute gallbladder event is suspected, interrupt REZDIFFRA treatment until the event is resolved [see Adverse Reactions (6.1)].

5.3 Drug Interaction with Certain Statins

An increase in exposure of atorvastatin, pravastatin, rosuvastatin and simvastatin was observed when concomitantly administered with REZDIFFRA [see Clinical Pharmacology (12.3)], which may increase the risk of adverse reactions related to these drugs. Dosage adjustment for certain statins is recommended [see Drug Interactions (7.2)]. Monitor for statin-related adverse reactions including but not limited to elevation of liver tests, myopathy, and rhabdomyolysis.

6 ADVERSE REACTIONS

The following clinically significant adverse reactions are described elsewhere in labeling:

- Hepatotoxicity [see Warnings and Precautions (5.1)]
- Gallbladder-Related Adverse Reactions [see Warnings and Precautions (5.2)]

6.1 Clinical Trials Experience

Because clinical trials are conducted under widely varying conditions, adverse reaction rates observed in the clinical trials of a drug cannot be directly compared with rates in clinical trials of another drug and may not reflect the rates observed in clinical practice.

The safety of REZDIFFRA was evaluated in two randomized, double-blind, placebo-controlled trials that enrolled a total of 2019 patients.

Trial 1

Trial 1 included patients who had noncirrhotic NASH with stages F2 and F3 fibrosis at eligibility (n=888) [see Clinical Studies (14)].

Adverse Reactions Leading to Discontinuations

The exposure-adjusted incidence rates (EAIRs) per 100 person-years (PY) for treatment discontinuation due to any adverse reaction were higher in the REZDIFFRA dosage arms: 4 per 100 PY, 5 per 100 PY, and 8 per 100 PY in placebo, REZDIFFRA 80 mg once daily, and REZDIFFRA 100 mg once daily arms, respectively. Diarrhea and nausea were the most common causes of treatment discontinuation.

Common Adverse Reactions

Table 1 displays EAIRs per 100 PY for the common adverse reactions that occurred in at least 5% of patients with F2 or F3 fibrosis treated in either drug arm with REZDIFFRA and were greater than that reported for placebo.

Table 1: Exposure-Adjusted Incidence Rates (EAIR) of Common Adverse Reactions Reported with REZDIFFRA in Adult Patients with Noncirrhotic NASH (Trial 1)a, b, c
Adverse Reaction | Placebo; N=294; n (EAIRd) | REZDIFFRA 80 mg Once; Daily; N=298; n (EAIRd) | REZDIFFRA 100 mg; Once Daily; N=296; n (EAIRd)
Diarrhea | 52 (14) | 78 (23) | 98 (33)
Nausea | 36 (9) | 65 (18) | 51 (15)
Pruritus | 18 (4) | 24 (6) | 36 (10)
Vomiting | 15 (4) | 27 (7) | 30 (8)
Constipation | 18 (4) | 20 (5) | 28 (8)
Abdominal pain | 18 (4) | 22 (5) | 27 (7)
Dizziness | 6 (1) | 17 (4) | 17 (4)
a Population includes adult patients with noncirrhotic NASH with liver fibrosis (stages F2 and F3 at eligibility).
b Median exposure duration was 68 weeks for placebo, 74 weeks for REZDIFFRA 80 mg once daily, and 66 weeks for
REZDIFFRA 100 mg once daily.
c EAIRs are per 100 person-years (PY) where total PYs were 435, 435, and 407 for placebo, 80 mg once daily, and 100
mg once daily arms, respectively.
d The EAIR per 100 PY can be interpreted as an estimated number of first occurrences of the adverse reaction of interest
if 100 patients are treated for one year.
Abbreviations: EAIR, exposure-adjusted incidence rate; PY, person-years; NASH, nonalcoholic steatohepatitis

Gastrointestinal Adverse Reactions

The incidence of gastrointestinal adverse reactions was higher for the REZDIFFRA drug arms compared to placebo. The EAIRs for gastrointestinal adverse reactions were 57 per 100 PY, 73 per 100 PY, and 89 per 100 PY in the placebo, REZDIFFRA 80 mg once daily, REZDIFFRA 100 mg once daily arms, respectively.

Diarrhea typically began early in treatment initiation and was mild to moderate in severity. The median time (Q1 to Q3) to a diarrheal event was 39 (2 to 195) days, 17 (3 to 70) days, and 6 (2 to 54) days in the placebo, REZDIFFRA 80 mg once daily, and REZDIFFRA 100 mg once daily arms, respectively.

Median duration of diarrhea was 9 days for placebo compared to 20 days for both REZDIFFRA 80 mg once daily and REZDIFFRA 100 mg once daily dosage arms.

Nausea also began early in treatment and was mild to moderate in severity. Among patients with nausea, the median time (Q1 to Q3) to a nausea event was 85 (24 to 347) days, 28 (2 to 162) days, and 5 (2 to 40) days in the placebo, REZDIFFRA 80 mg once daily, and REZDIFFRA 100 mg once daily arms, respectively. Median duration of nausea was 17 days, 26 days, and 28 days for patients in the placebo, REZDIFFRA 80 mg once daily, and REZDIFFRA 100 mg once daily arms, respectively.

Vomiting and abdominal pain adverse reactions were mild to moderate in severity.

Hypersensitivity Reactions

Reactions such as urticaria and rash, which may reflect drug hypersensitivity, were observed in patients receiving REZDIFFRA. The EAIRs for urticaria were 0.2 per 100 PY, 0.7 per 100 PY, and 1.5 per 100 PY in the placebo, REZDIFFRA 80 mg once daily, and REZDIFFRA 100 mg once daily arms, respectively. The EAIRs for rash were 3 per 100 PY in the placebo and REZDIFFRA 80 mg once daily arms compared to 5 per 100 PY in the REZDIFFRA 100 mg once daily arm.

Gallbladder-Related Adverse Reactions

A higher incidence of cholelithiasis, acute cholecystitis, and obstructive pancreatitis (gallstone) was observed in the treatment arms compared to placebo. However, the EAIRs for these events were less than 1 per 100 PY for all treatment arms.

Less Common Adverse Reactions

Additional adverse reactions that occurred more frequently in the REZDIFFRA arms compared to placebo, in less than 5% of patients, included decreased appetite, flatulence, abnormal feces, dysgeusia, vertigo, arrhythmia, palpitations, depression, erythema, hypoglycemia, tendinopathy, abnormal uterine bleeding.

Laboratory Abnormalities

Liver Tests

Increases in mean alanine aminotransferase (ALT) and aspartate aminotransferase (AST) levels were observed in the first 4 weeks after initiating treatment with REZDIFFRA. In both REZDIFFRA dosage arms, the mean elevation in ALT and AST values was less than 1.5 times baseline at 4 weeks after treatment initiation. These values returned to baseline around 8 weeks after initiating treatment.

Table 2 presents the frequency of liver test elevations during Trial 1.

Table 2: Frequency of Liver Test Elevations in Trial 1
 | Placebo; (%) | REZDIFFRA 80 mg; Once Daily; (%) | REZDIFFRA 100; mg Once Daily; (%)
ALT > 3x ULN | 10 | 11 | 13
ALT > 5x ULN | 2 | 2 | 2
AST > 3x ULN | 10 | 9 | 12
AST > 5x ULN | 2 | 1 | 4
TBa > 2x ULN | 2 | 1 | 3
a TB elevations include patients with Gilbert syndrome.

Thyroid Function Tests

A decrease in levels of prohormone free T4 (FT4) of mean 2%, 13%, and 17% was seen at 12 months in patients treated with placebo, REZDIFFRA 80 mg once daily, and REZDIFFRA 100 mg once daily, respectively, with minimal changes in active hormone T3 or in TSH. There were no clinical findings associated with FT4 decreases.

Additional Safety Data

The safety evaluation of REZDIFFRA also included an analysis of an additional randomized placebo-controlled safety trial which included 969 patients from a relevant patient population (placebo [n=318], REZDIFFRA 80 mg once daily [n=327], and REZDIFFRA 100 mg once daily [n=324]).

Data from the safety trial was combined with data from NASH patients with F2 and F3 fibrosis at eligibility (n=888) and data from an additional 162 patients from a relevant patient population enrolled in Trial 1. In the combined safety population (n=2019), the median (Q1 to Q3) age of patients at baseline was 58 (50 to 65) years; 55% were female, 28% were Hispanic, 89% were White, 2% were Asian, and 4% were Black or African American.

The safety profile from this combined analysis was similar to that in Trial 1, other than the one case of hepatotoxicity in the safety trial [see Warnings and Precautions (5.1)].

7 DRUG INTERACTIONS

7.1 Effects of Strong or Moderate CYP2C8 Inhibitors on REZDIFFRA

Table 3 includes clinically significant drug interaction effects of strong or moderate CYP2C8 inhibitors on REZDIFFRA.

Table 3: Clinically Significant Interaction Effects of Strong or Moderate CYP2C8 Inhibitors on REZDIFFRA
Clinical Impact | Resmetirom is a CYP2C8 substrate. Concomitant use with a strong or moderate CYP2C8 inhibitor can increase resmetirom Cmax and AUC [see Clinical Pharmacology (12.3)], which may increase the risk of REZDIFFRA adverse reactions.
Intervention | Concomitant use of REZDIFFRA with strong CYP2C8 inhibitors (e.g., gemfibrozil) is not recommended. Reduce REZDIFFRA dosage if used concomitantly with a moderate CYP2C8 inhibitor (e.g., clopidogrel) [see Dosage and Administration (2.2)].

7.2 Effects of REZDIFFRA on Other Drugs

Table 4 includes clinically significant drug interactions affecting other drugs.

Table 4: Clinically Significant Interactions Affecting Other Drugs
Statins (Atorvastatin, Pravastatin, Rosuvastatin, or Simvastatin)
Clinical Impact | REZDIFFRA increased plasma concentrations of some statins (atorvastatin, pravastatin, rosuvastatin and simvastatin) [see Clinical Pharmacology (12.3)], which may increase the risk of adverse reactions related to these drugs.
Intervention | Rosuvastatin and simvastatin: Limit daily statin dosage to 20 mg. Pravastatin and atorvastatin: Limit daily statin dosage to 40 mg.
CYP2C8 Substrates
Clinical Impact | Resmetirom is a weak CYP2C8 inhibitor. Resmetirom increases exposure of CYP2C8 substrates [see Clinical Pharmacology (12.3)], which may increase the risk of adverse reactions related to these substrates.
Intervention | Monitor patients more frequently for substrate-related adverse reactions if REZDIFFRA is co-administered with CYP2C8 substrates where minimal concentration changes may lead to serious adverse reactions.

8 USE IN SPECIFIC POPULATIONS

8.1 Pregnancy

Risk Summary

There are no available data on REZDIFFRA use in pregnant women to evaluate for a drug-associated risk of major birth defects, miscarriage, or other adverse maternal or fetal outcomes. There are risks to the mother and fetus related to underlying NASH with liver fibrosis (see Clinical Considerations). In animal reproduction studies, adverse effects on embryo-fetal development occurred in pregnant rabbits treated with resmetirom at 3.5 times the maximum recommended dose during organogenesis. These effects were associated with maternal toxicity, whereas no embryo-fetal effects were observed at lower dose levels with better tolerance in pregnant rabbits. No embryo-fetal developmental effects occurred in pregnant rats treated with resmetirom or the metabolite MGL-3623. A pre- and postnatal development study in rats with maternal dosing of resmetirom during organogenesis through lactation showed a decrease in birthweight and increased incidence of stillbirths and mortality (postnatal days 1-4) at 37 times the maximum recommended dose (see Data). These effects were associated with marked suppression of maternal T4, T3, and TSH levels.

The background risk of major birth defects and miscarriage for the indicated population is unknown. All pregnancies have a background risk of birth defect, loss, and other adverse outcomes. In the U.S. general population, the estimated background risk of major birth defects and miscarriage in clinically recognized pregnancies is 2 to 4% and 15 to 20%, respectively.

Report pregnancies to Madrigal Pharmaceuticals, Inc. Adverse Event reporting line at 1-800-905-0324 or https://pregnancyregistry.madrigalpharma.com.

Clinical Considerations

Disease-Associated Maternal and/or Embryo/Fetal Risk

There are risks to the mother and fetus related to underlying maternal NASH with liver fibrosis, such as increased risks of gestational diabetes, hypertensive complications, preterm birth, and postpartum hemorrhage.

Data

Animal Data

No effects on embryo-fetal development were observed in pregnant rats treated orally with up to 100 mg/kg/day (21 times the maximum recommended dose based on AUC [area under the plasma concentration-time curve]) or in pregnant rabbits treated orally with up to 30 mg/kg/day (2.8 times the maximum recommended dose based on AUC) during the period of organogenesis. Oral administration of 75 mg/kg/day in pregnant rabbits (3.5 times the maximum recommended dose based on AUC) produced an increase in post-implantation loss and decreases in viable fetuses and fetal weight. These effects were likely due to maternal toxicity (i.e., marked reductions in weight gain and food consumption).

A pre- and postnatal development study was performed using oral administration of 3, 30, or 100 mg/kg/day in female rats during organogenesis through lactation. Treatment with 100 mg/kg/day (37 times the maximum recommended dose based on AUC) produced increases in number of stillborn, pup deaths during postnatal days 1-4, and pups with absence of milk in stomach. Birthweight was decreased by 10% in this dose group, with recovery to normal body weight thereafter. The effects in offspring were associated with marked reductions in maternal plasma levels of T4 (88% decrease), T3 (79% decrease), and TSH (44% decrease). No effects on postnatal development were observed at doses up to 30 mg/kg/day (7.2 times the maximum recommended dose based on AUC). This study lacked a complete evaluation of physical and neurobehavioral development in offspring; however, no effects of resmetirom were noted in tests of learning and memory.

The metabolite MGL-3623 was tested for its effects on embryo-fetal development. No effects were observed in pregnant rats treated orally with up to 100 mg/kg/day MGL-3623 (4.7 times the maximum recommended dose based on AUC for MGL-3623) during the period of organogenesis.

8.2 Lactation

Risk Summary

There is no information regarding the presence of REZDIFFRA in human or animal milk, the effects on the breast-fed infant, or the effects on milk production. The developmental and health benefits of breastfeeding should be considered along with the mother's clinical need for REZDIFFRA and any potential adverse effects on the breastfed infant from REZDIFFRA or from the underlying maternal condition.

8.4 Pediatric Use

The safety and effectiveness of REZDIFFRA have not been established in pediatric patients.

8.5 Geriatric Use

In Trial 1, of the 594 patients with NASH who received at least one dose of REZDIFFRA, 149 (25%) were 65 years of age and older and 13 (2%) were 75 years of age and older [see Clinical Studies (14)]. No overall differences in effectiveness but numerically higher incidence of adverse reactions have been observed in patients 65 years of age and older compared to younger adult patients.

8.6 Renal Impairment

The recommended dosage of REZDIFFRA in patients with mild, moderate, or severe renal impairment is the same as in patients with normal kidney function [see Clinical Pharmacology (12.3)].

8.7 Hepatic Impairment

Avoid use of REZDIFFRA in patients with decompensated cirrhosis (consistent with moderate to severe hepatic impairment). Moderate or severe hepatic impairment (Child-Pugh Class B or C) increases resmetirom Cmax and AUC [see Clinical Pharmacology (12.3)], which may increase the risk of adverse reactions.

No dosage adjustment is recommended for patients with mild hepatic impairment (Child-Pugh Class A) [see Clinical Pharmacology (12.3)].

The safety and effectiveness of REZDIFFRA have not been established in patients with NASH cirrhosis.

11 DESCRIPTION

REZDIFFRA (resmetirom) tablets contain resmetirom, a thyroid hormone receptor-beta agonist. The chemical name for REZDIFFRA is 2-[3,5-Dichloro-4-((6-oxo-5-(propan-2-yl)-1,6-dihydropyridazin-3-yl)oxy)phenyl]-3,5-dioxo-2,3,4,5-tetrahydro-1,2,4-triazine-6-carbonitrile. The molecular formula is C17H12Cl2N6O4 and the molecular weight is 435.22. The chemical structure is:

Resmetirom has low aqueous solubility below pH 6 and higher solubility above pH 7 (0.44 mg/mL at pH 7.04).

REZDIFFRA tablets are supplied in 60 mg, 80 mg, and 100 mg strengths for oral administration. Each tablet contains the active ingredient, resmetirom, and the following USP/NF excipients: colloidal silicon dioxide, croscarmellose sodium, magnesium stearate, mannitol, and microcrystalline cellulose. REZDIFFRA tablets are film-coated with an Opadry coating comprised of polyethylene glycol, polyvinyl alcohol, talc, titanium dioxide, red iron oxide (100 mg tablets), yellow iron oxide (80 mg and 100 mg tablets).

12 CLINICAL PHARMACOLOGY

12.1 Mechanism of Action

Resmetirom is a partial agonist of the thyroid hormone receptor-beta (THR-β). Resmetirom produced 83.8% of the maximum response compared to triiodothyronine (T3), with an EC50 of 0.21 µM in an in vitro functional assay for THR-β activation. The same functional assay for thyroid hormone receptor-alpha (THR-α) agonism showed 48.6% efficacy for resmetirom relative to T3, with an EC50 of 3.74 µM. THR-β is the major form of THR in the liver, and stimulation of THR-β in the liver reduces intrahepatic triglycerides, whereas actions of thyroid hormone outside the liver, including in heart and bone, are largely mediated through THR-α.

12.2 Pharmacodynamics

Liver Fat Content

Resmetirom decreases liver fat content as measured by magnetic resonance imaging-protein density fat fraction (MRI-PDFF) or FibroScan controlled attenuation parameter (CAP).

Reductions in liver fat content by MRI-PDFF were observed at 16 (the first assessment) and 52 weeks of treatment. Reductions in liver fat content by CAP were observed at 52 weeks of treatment.

Prohormone FT4

Resmetirom decreased concentrations of prohormone FT4 were observed at the first assessment at 4 weeks of treatment. Similar decreases in FT4 were observed during the treatment [see Adverse Reactions (6.1)].

Sex Hormone Binding Globulin (SHBG)

Resmetirom increased concentrations of sex hormone binding globulin (SHBG) were observed at the first assessment at 4 weeks of treatment, and at longer durations of treatment. The clinical significance of this change is unknown.

Cardiac Electrophysiology

At a dose two times the maximum recommended dose, resmetirom does not prolong the QT interval to any clinically relevant extent.

12.3 Pharmacokinetics

Following once daily doses, steady state is typically reached within 3 to 6 days of dosing. Resmetirom steady state exposure increases in a dose proportional manner between doses of 40 mg (0.5 times the lowest approved recommended dose) and 100 mg. Resmetirom exposure increases in a greater than dose proportional manner between doses of 100 mg and 200 mg (2 times the highest approved recommended dose) by about 5.6-fold. Resmetirom exposure increased 1.5- to 3-fold following once daily dosing; however, the MGL-3623 metabolite does not accumulate. The estimated resmetirom systemic exposure at steady state in NASH patients is summarized in Table 5. Resmetirom exposure is similar between NASH patients with F2 stage fibrosis and F3 stage fibrosis.

Table 5: Resmetirom Estimated Systemic Exposure at Steady State in Patients with NASH with Fibrosis (F2 and F3)
Parameter | Resmetirom 80 mg; Once Daily; Mean (CV%) | Resmetirom 100 mg; Once Daily; Mean (CV%)
Cmax,ss (ng/mL)a | 778 (41.5) | 971 (40.9)
AUCtau,ss (ng*h/mL)a | 5850 (60.5) | 7780 (65.5)
Abbreviations: AUCtau,ss = area under the concentration-versus-time curve over one dosing interval at steady state; Cmax,ss = maximum concentration at steady state; CV = arithmetic coefficient of variation

Absorption

The resmetirom median time to maximum plasma concentration (Tmax) is approximately 4 hours following multiple daily doses of resmetirom 80 mg or 100 mg.

Effect of Food

No clinically significant differences in resmetirom pharmacokinetics were observed following administration with a high-fat meal (approximately 150, 250, and 500-600 calories from protein, carbohydrate, and fat, respectively). Concomitant food administration resulted in a 33% decrease in Cmax, an 11% decrease in AUC, and a delay in median Tmax by about 2 hours compared to under fasted condition.

Distribution

Resmetirom apparent volume of distribution (Vd/F) at steady-state is 68 (227%) L. Resmetirom is greater than 99% protein-bound.

Elimination

Resmetirom median terminal plasma half-life (t½) is 4.5 hours and the steady state apparent clearance (CL/F) is 17.5 (56.3%) L/h.

Metabolism

Resmetirom is metabolized by CYP2C8 and is not metabolized by other CYP enzymes in vitro.

MGL-3623 is a major metabolite with a 28-times lower potency for THR-β than resmetirom. MGL-3623 represents 33% to 51% of resmetirom AUC at steady state following administration of 100 mg once daily.

Excretion

Following oral administration of a 100 mg radio-labeled dose of resmetirom, approximately 67% of the total radioactive dose was recovered in the feces, mostly as metabolites and 24% of the total radioactive dose was recovered in the urine. Unchanged labeled resmetirom was not detected in feces and accounted for 1% of the dose recovered in urine. A metabolite MGL-3623 accounted for 3.3% and 16% of the dose recovered in feces and urine, respectively. Oxalic acid metabolite was observed in plasma but not in urine.

Specific Populations

No clinically significant differences in the pharmacokinetics of resmetirom were observed based on age (18 to 83 years), sex, race (White, Black, or Asian), or ABCG2 genotype (BCRP p.Gln141Lys, p.Val12Met).

Population PK analyses indicated no clinically significant difference in the pharmacokinetics of resmetirom by mild to moderate renal impairment (eGFR 30 to 89 mL/min/1.73 m^2, Modification of Diet in Renal Disease (MDRD)). In subjects with severe renal impairment (eGFR <30 mL/min/1.73 m², CKD-EPI), repeated 100 mg once daily dosing of resmetirom resulted in an approximately 1.5-fold increase in resmetirom AUC and a 1.3-fold increase in resmetirom Cmax compared to matched healthy subjects. In the same study, MGL-3623 AUCtau was 1.4-fold higher and Cmax was 1.06-fold higher in patients with severe renal impairment, compared to subjects with normal renal function.

Body Weight

A clinically significant difference in resmetirom exposure was not observed with the recommended weight-based dosage. However, resmetirom CL/F and Vd/F increase with increasing body weight, resulting in lower resmetirom exposure in patients with higher body weight receiving the same dosage as lower weight patients [see Dosage and Administration (2.1)].

Patients with Hepatic Impairment

Patients with Hepatic Impairment: Following repeated 80 mg once daily dosing of resmetirom for 6 days, resmetirom AUC was 1.3-fold, 2.7-fold and 19-fold higher in patients with mild, moderate and severe hepatic impairment (Child-Pugh A, B and C), respectively compared to subjects with normal hepatic function. Resmetirom Cmax was 1.2-fold, 1.7-fold and 8.1-fold higher in patients with mild, moderate and severe hepatic impairment, respectively, compared to subjects with normal hepatic function (Table 6).

In the same study, MGL-3623 AUCtau was 1.3-fold, 2-fold and 5.8-fold higher in patients with mild, moderate and severe hepatic impairment, respectively, compared to subjects with normal hepatic function [see Use in Specific Populations (8.7)].

Table 6: Mean (CV%) Resmetirom Systemic Exposure in Subjects with Normal Hepatic Function and Non-NASH Patients with Hepatic Impairment Following Resmetirom 80 mg Once Daily for 6 Days and Exposure Change Relative to Normal Hepatic Function
Parameter | Normal; Hepatic; Function; (N = 7) | Child-Pugh Class
Parameter | Normal; Hepatic; Function; (N = 7) | A; Mild; (N = 10) | B; Moderate; (N = 9) | C; Severe; (N = 3)
 | Resmetirom
Cmax,ss (ng/mL)a | 1070 (51.0) | 1390 (67.8) | 1830 (47.5) | 7730 (17.4)
AUCtau,ss (ng*h/mL)a | 5100 (51.5) | 5570 (66.4) | 15100 (65.8)b | 97600 (39.0)
a Exposure parameters presented as Mean (CV%)
b N = 8
Abbreviations: AUCtau,ss = area under the concentration-versus-time curve over one dosing interval at steady state; Cmax,ss = maximum concentration at steady state; CV = arithmetic coefficient of variation

NASH Patients with Mild Hepatic Impairment (Child-Pugh A): Geometric mean AUC and Cmax in NASH cirrhosis patients with mild hepatic impairment (Child-Pugh Class A; n = 20) were 6% higher and 10% lower, respectively, compared to non-cirrhotic NASH patients following repeated 100 mg once daily dosing of resmetirom for 6 days. The safety and effectiveness of resmetirom have not been established in patients with NASH cirrhosis.

Drug Interaction Studies

Clinical Studies

Moderate CYP2C8 Inhibitors: Resmetirom Cmax increased 1.3-fold and AUC 1.7-fold following concomitant use of multiple doses of resmetirom 100 mg/day with clopidogrel (a moderate CYP2C8 inhibitor) at steady-state in healthy subjects [see Drug Interactions (7.1)].

CYP2C8 Substrates: Pioglitazone (a CYP2C8 substrate) Cmax was unchanged and AUC increased 1.5-fold following concomitant use of a single oral dose of pioglitazone (15 mg) with resmetirom at steady state (100 mg/day) in healthy subjects [see Drug Interactions (7.1)].

Simvastatin: Simvastatin (OATP1B1 and OATP1B3 substrate) Cmax increased 1.4-fold and AUC 1.7- fold following concomitant use of a single oral dose of simvastatin (20 mg) with resmetirom at steady state (100 mg/day) in healthy subjects [see Drug Interactions (7.2)].

Rosuvastatin: Rosuvastatin (BCRP, OATP1B1, and OATP1B3 substrate) Cmax increased 1.8-fold and AUC 1.4-fold following concomitant use of a single oral dose of rosuvastatin (20 mg) with resmetirom at steady state (100 mg/day) in healthy subjects [see Drug Interactions (7.2)].

Pravastatin: Pravastatin (OATP1B1 and OATP1B3 substrate) Cmax increased 1.3-fold and AUC 1.4-fold following concomitant use of a single oral dose of pravastatin (40 mg) with resmetirom at steady state (100 mg/day) in healthy subjects [see Drug Interactions (7.2)].

Atorvastatin: Atorvastatin (BCRP, OATP1B1, and OATP1B3 substrate) Cmax was unchanged and AUC increased 1.4-fold following concomitant use of a single oral dose of atorvastatin (20 mg) with resmetirom at steady state (100 mg/day) in healthy subjects. Atorvastatin lactone Cmax increased 2.0-fold and AUC increased 1.8-fold [see Drug Interactions (7.2)].

OATP1B1, OATP1B3 and BCRP inhibitors: No clinically significant differences in the pharmacokinetics of resmetirom were observed when used concomitantly with cyclosporine (an OATP1B1/1B3 and BCRP inhibitor).

Other Drugs: No clinically significant differences in the pharmacokinetics of R-warfarin or S-warfarin were observed when used concomitantly with resmetirom.

In Vitro Studies

CYP450 Enzymes: Resmetirom is an inhibitor of CYP2C8.

Glucuronidation Enzymes: Resmetirom is an inhibitor of UDP-glucuronosyltransferases (UGTs) 1A4 and 1A9. The clinical relevance of UGT1A4 and UGT1A9 inhibition is unknown.

Transporters: Resmetirom is a substrate for organic anion-transporting polypeptides (OATP) 1B1 and 1B3 and breast cancer resistance protein (BCRP). Resmetirom inhibits OATP1B1, OATP1B3, BCRP, OAT3, and bile salt export pump (BSEP). The clinical significance of OAT3 and BSEP inhibition is unknown.

13 NONCLINICAL TOXICOLOGY

13.1 Carcinogenesis, Mutagenesis, Impairment of Fertility

Carcinogenesis

In a 2-year study in CD-1 mice, resmetirom produced leiomyoma or leiomyosarcoma in the uterus at a dose of 100 mg/kg/day (51 times the maximum recommended dose based on AUC). No tumorigenic effects were observed in female mice at doses of up to 30 mg/kg/day (14 times the maximum recommended dose based on AUC) or in male mice at doses of up to 100 mg/kg/day (35 times the maximum recommended dose based on AUC).

In a 2-year study in Sprague-Dawley rats, resmetirom produced benign fibroadenoma in the mammary gland of males at a dose of 30 mg/kg/day (6.5 times the maximum recommended dose based on AUC). No tumorigenic effects were observed in male rats at doses of up to 6 mg/kg/day (3.7 times the maximum recommended dose based on AUC) or in female rats at doses of up to 30 mg/kg/day (3.4 times the maximum recommended dose based on AUC).

In a 26-week study in transgenic [CByB6F1-Tg(HRAS)2Jic] mice, the major metabolite of resmetirom, MGL-3623, was not tumorigenic at doses of up to 1500 mg/kg/day.

Mutagenesis

Resmetirom was negative in the in vitro bacterial reverse mutation (Ames) assay, the in vitro chromosomal aberration assay in human peripheral blood lymphocytes, the in vitro micronucleus assay in L5178Y tk+/- mouse lymphoma cells, and the in vivo rat micronucleus assay.

The metabolite MGL-3623 was negative in the in vitro bacterial reverse mutation (Ames) assay and the in vivo rat micronucleus assay. MGL-3623 tested positive in the presence of metabolic activation in the in vitro micronucleus assay with TK6 human lymphoblast cells, with the increase in micronuclei limited to a single concentration that produced 59% growth inhibition.

Impairment of Fertility

Resmetirom had no effects on fertility or reproductive function in male and female rats at oral doses of up to 30 mg/kg/day (6.9 times and 2.6 times the maximum recommended dose in male and female rats, respectively, based on AUC).

14 CLINICAL STUDIES

The efficacy of REZDIFFRA was evaluated based on an efficacy analysis at Month 12 in Trial 1 (NCT03900429), a 54-month, randomized, double-blind, placebo-controlled trial. Enrolled patients had metabolic risk factors and a baseline or recent liver biopsy showing NASH with fibrosis stage 2 or 3 and a NAFLD Activity Score (NAS) of at least 4. Efficacy determination was based on the effect of REZDIFFRA on resolution of steatohepatitis without worsening of fibrosis and one stage improvement in fibrosis without worsening of steatohepatitis, on post-baseline liver biopsies collected at 12 months.

The month 12 analysis included 888 F2 and F3 (at eligibility) patients randomized 1:1:1 to receive placebo (n = 294), REZDIFFRA 80 mg once daily (n = 298), or REZDIFFRA 100 mg once daily (n = 296), in addition to lifestyle counseling on nutrition and exercise. Patients were on stable doses of medications for diabetes, dyslipidemia, and hypertension.

Demographic and baseline characteristics were balanced between treatment and placebo groups. Overall, the median (Q1 to Q3) age of patients at baseline was 58 (51 to 65) years, 56% were female, 21% were Hispanic, 89% were White, 3% were Asian, and 2% were Black or African American. Median (Q1 to Q3) body mass index (BMI) was 35 (31 to 40) kg/m^2 and median (Q1 to Q3) body weight was 99 (85 to 114) kg. Baseline characteristics are presented in Table 7.

Table 7: Baseline Characteristics in Adult Patients with Noncirrhotic NASH with Stage 2 to Stage 3 Fibrosis in Trial 1
Characteristic | Overall; N=888
Fibrosis stage, n (%); F2; F3
Fibrosis stage, n (%); F2; F3 | 328 (37); 560 (63)
Type 2 Diabetes, n (%) | 608 (68)
Hypertension, n (%) | 700 (79)
Dyslipidemia, n (%) | 633 (71)
Statin use, n (%) | 434 (49)
Thyroxine use, n (%) | 124 (14)
Vibration-controlled Transient Elastography (VCTE) (kPa), Median (Q1, Q3)a, b | 12 (10, 15)
Controlled attenuation parameter (CAP) (Db/M), Median (Q1, Q3)a | 349 (320, 378)
Fibrosis Index Based on 4 Factors (FIB-4), Median (Q1, Q3)a | 1.3 (1, 1.8)
Enhanced Liver Fibrosis (ELF), Median (Q1, Q3)a | 9.7 (9.2, 10.4)
a Less than 5% missingness in these variables is omitted.
b kPa = kilopascal; Db/M = decibels per meter

Table 8 presents the Month 12 histopathology results comparing REZDIFFRA with placebo on 1) the percentage of patients with resolution of steatohepatitis and no worsening of liver fibrosis and 2) the percentage of patients with at least one stage improvement in liver fibrosis and no worsening of steatohepatitis. Two pathologists, Pathologist A and Pathologist B, independently read the liver biopsies for each patient. Both the 80 mg once daily and the 100 mg once daily dosages of REZDIFFRA demonstrated improvement on these histopathology endpoints at Month 12 compared to placebo. In a statistical analysis incorporating both pathologists’ independent readings, REZDIFFRA achieved statistical significance on both histopathology endpoints for both doses.

Examination of age, gender, diabetes status (Yes or No), and fibrosis stage (F2 or F3) subgroups did not identify differences in response to REZDIFFRA among these subgroups. The majority of patients in the trial were white (89%); there were too few patients of other races to adequately assess differences in response by race.

Table 8: Efficacy Results at Month 12 in Adult Patients with Noncirrhotic NASH with Stage 2 or Stage 3 Fibrosis in Trial 1
 | Placebo; N=294 | REZDIFFRA; 80 mg; Once Daily; N=298 | REZDIFFRA; 100 mg; Once Daily; N=296
Resolution of steatohepatitis and no worsening of liver fibrosis
Response rate, Pathologist A (%) | 13 | 27 | 36
Difference in response rate vs. placebo (95% CI) |  | 14 (8, 20) | 23 (16, 30)
Response rate, Pathologist B (%) | 9 | 26 | 24
Difference in response rate vs. placebo (95% CI) |  | 17 (11, 23) | 15 (9, 21)
Improvement in liver fibrosis and no worsening of steatohepatitis
Response rate, Pathologist A (%) | 15 | 23 | 28
Difference in response rate vs. placebo (95% CI) |  | 8 (2, 14) | 13 (7, 20)
Response rate, Pathologist B (%) | 13 | 23 | 24
Difference in response rate vs. placebo (95% CI) |  | 11 (5, 17) | 11 (5, 17)
Liver fibrosis was evaluated on the NASH Clinical Research Network (CRN) fibrosis score as 0 to 4. Resolution of steatohepatitis was defined as a score of 0–1 for inflammation, 0 for ballooning, and any value for steatosis. No worsening of steatohepatitis was defined as no increase in score for ballooning, inflammation, or steatosis. Estimated using the Mantel-Haenszel method stratified by baseline type 2 diabetes status (presence or absence) and fibrosis stage (F2 or F3). 95% stratified Newcombe confidence intervals (CIs) are provided. Patients with missing liver biopsy at Month 12 are considered a non-responder.

Starting at Month 3 and through Month 12, there was a trend of greater reductions from baseline in average ALT and AST in the REZDIFFRA groups as compared to the placebo group.

16 HOW SUPPLIED/STORAGE AND HANDLING

How Supplied

REZDIFFRA (resmetirom) tablets are packaged in white high-density polyethylene bottles closed with a child-resistant closure containing an induction seal.

60 mg Tablets: white oval-shaped film-coated tablets, debossed “P60” on one side and plain on the other side.

- Bottle of 30 count (NDC 82576-060-30)

80 mg Tablets: yellow, oval-shaped, film-coated tablets, debossed with “P80” on one side and plain on the other side.

- Bottle of 30 count (NDC 82576-080-30)
- Bottle of 90 count (NDC 82576-080-90)

100 mg Tablets: beige to pink, oval-shaped, film-coated tablets, debossed with “P100” on one side and plain on the other side.

- Bottle of 30 count (NDC 82576-100-30)
- Bottle of 90 count (NDC 82576-100-90)

Storage and Handling

Store at 20°C to 25°C (68°F to 77°F); excursions permitted to 15°C to 30°C (59°F to 86°F) [see USP Controlled Room Temperature].

17 PATIENT COUNSELING INFORMATION

Advise the patient to read the FDA-approved patient labeling (Patient Information).

Administration Instructions
Instruct patients to swallow REZDIFFRA tablets whole and not split, crush, or chew tablets [see Dosage and Administration (2.1)].

Hepatotoxicity

Inform patients of the risk of hepatotoxicity. Instruct patients to immediately report any signs or symptoms of severe liver injury (e.g., fatigue, nausea, vomiting, right upper quadrant pain or tenderness, jaundice, fever, rash) to their healthcare provider [see Warnings and Precautions (5.1)].

Gallbladder-Related Adverse Reactions

Inform patients of the potential risk for cholelithiasis, cholecystitis, and obstructive pancreatitis (gallstones) during treatment with REZDIFFRA. Instruct patients to contact their healthcare provider if they develop signs or symptoms of these conditions [see Warnings and Precautions (5.2)].

Drug Interaction with Statins

Inform patients that concomitant use of REZDIFFRA with some statins may increase the risk of statin- related adverse reactions (e.g., elevation of liver tests, myopathy, rhabdomyolysis) [see Warnings and Precautions (5.3), Drug Interactions (7.2)].

Pregnancy

Inform patients that there is a pregnancy safety study that monitors pregnancy outcomes in women exposed to REZDIFFRA during pregnancy. Encourage patients to report their pregnancy by visiting https://pregnancyregistry.madrigalpharma.com or calling 1-800-905-0324 [see Use in Specific Populations (8.1)].

Manufactured for and Distributed by:

Madrigal Pharmaceuticals, Inc.

West Conshohocken, PA

REZDIFFRA™ (resmetirom)

© 2025 Madrigal Pharmaceuticals, Inc.

PATIENT INFORMATION

REZDIFFRA (rez di' frah)

(resmetirom)

tablets, for oral use

What is REZDIFFRA?

REZDIFFRA is a prescribed medicine used along with diet and exercise to treat adults with nonalcoholic steatohepatitis (NASH) with moderate to advanced liver scarring (fibrosis), but not with cirrhosis of the liver.

It is not known if REZDIFFRA is safe and effective in children (under 18 years old).

Before you take REZDIFFRA, tell your healthcare provider about all of your medical conditions, including if you:

- have any liver problems other than NASH.
- have gallbladder problems or have been told you have gallbladder problems, including gallstones.
- are pregnant or plan to become pregnant. It is not known if REZDIFFRA will harm your unborn baby.
  - Pregnancy Safety Study. There is a pregnancy safety study for women who are or become pregnant during treatment with REZDIFFRA. The purpose of this pregnancy safety study is to collect information about your health and your baby’s health. You or your healthcare provider can report your pregnancy by visiting https://pregnancyregistry.madrigalpharma.com/ or calling 1-800-905-0324.
- are breastfeeding or plan to breastfeed. It is not known if REZDIFFRA passes into your breast milk. Talk to your healthcare provider about the best way to feed your baby if you take REZDIFFRA.

Tell your healthcare provider about all the medicines you take, including prescription and over-the-counter medicines, vitamins, and herbal supplements.

REZDIFFRA and other medicines may affect each other, causing side effects. REZDIFFRA may affect the way other medicines work, and other medicines may affect how REZDIFFRA works.

Especially tell your healthcare provider if you take medicines that contain gemfibrozil to help lower your triglycerides because REZDIFFRA is not recommended in patients taking these medicines.

Tell your healthcare provider if you are taking medicines such as clopidogrel to thin your blood or statin medicines to help lower your cholesterol.

Know the medicines you take. Keep a list of them to show your healthcare provider and pharmacist when you get a new medicine.

How should I take REZDIFFRA?

• Take REZDIFFRA exactly as your healthcare provider tells you to take it.

• Your dose of REZDIFFRA is based on your body weight.

• Take REZDIFFRA by mouth, 1 time a day with or without food.

• Swallow REZDIFFRA tablets whole. Do not split, crush, or chew tablets.

• If you miss a dose of REZDIFFRA, skip the missed dose and take your next dose at the regular time.

What are the possible side effects of REZDIFFRA?

REZDIFFRA may cause serious side effects, including:

• liver injury (hepatotoxicity). Stop taking REZDIFFRA and call your healthcare provider right away if you develop the following signs or symptoms of hepatotoxicity:

o tiredness o fever o pain or tenderness in the upper

o nausea o rash middle or upper right area of

o vomiting o your skin or the white part of your your stomach (abdomen)

eyes turns yellow (jaundice)

• gallbladder problems. Gallbladder problems such as gallstones, or inflammation of the gallbladder, or inflammation of the pancreas from gallstones can occur with NASH and may occur if you take REZDIFFRA. Call your healthcare provider right away if you develop any signs or symptoms of these conditions, including nausea, vomiting, fever, or pain in your stomach area (abdomen) that is severe and will not go away. The pain may be felt going from your abdomen to your back and the pain may happen with or without vomiting.

The most common side effects of REZDIFFRA include:

• diarrhea • itching • vomiting • constipation
• nausea • stomach (abdominal) pain • dizziness

These are not all the possible side effects of REZDIFFRA. For more information, ask your healthcare provider or pharmacist.

Call your doctor for medical advice about side effects. You may report side effects to FDA at 1-800-FDA-1088. You may also report side effects to www.fda.gov/medwatch.

How should I store REZDIFFRA?

- Store REZDIFFRA at room temperature between 68ºF to 77ºF (20ºC to 25ºC).

Keep REZDIFFRA and all medicines out of the reach of children.

General information about the safe and effective use of REZDIFFRA.

Medicines are sometimes prescribed for purposes other than those listed in a Patient Information leaflet. Do not use REZDIFFRA for a condition for which it was not prescribed. Do not give REZDIFFRA to other people, even if they have the same symptoms that you have. It may harm them.

You can ask your pharmacist or healthcare provider for information about REZDIFFRA that is written for health professionals.

What are the ingredients in REZDIFFRA?

Active ingredient: resmetirom

Inactive ingredients: colloidal silicon dioxide, croscarmellose sodium, magnesium stearate, mannitol, and microcrystalline cellulose. The film coating contains: polyethylene glycol, polyvinyl alcohol, talc, titanium dioxide, red iron oxide (100 mg tablets), and yellow iron oxide (80 mg and 100 mg tablets).

Manufactured for and Distributed by:

Madrigal Pharmaceuticals, Inc.

West Conshohocken, PA

This Patient Information has been approved by the U.S. Food and Drug Administration. Revised: 12/2025

PRINCIPAL DISPLAY PANEL – Bottle Label

NDC 82576-060-30

REZDIFFRA

(resmetirom) tablets

60 mg

Rx Only

30 Tablets

PRINCIPAL DISPLAY PANEL – Carton Label

NDC 82576-060-30

REZDIFFRA

(resmetirom) tablets

60 mg

Rx Only

30 Tablets

PRINCIPAL DISPLAY PANEL – Bottle Label

NDC 82576-080-30

REZDIFFRA

(resmetirom) tablets

80 mg

Rx Only

30 Tablets

PRINCIPAL DISPLAY PANEL – Carton Label

NDC 82576-080-30

REZDIFFRA

(resmetirom) tablets

80 mg

Rx Only

30 Tablets

PRINCIPAL DISPLAY PANEL – Bottle Label

NDC 82576-080-90

REZDIFFRA

(resmetirom) tablets

80 mg

Rx Only

90 Tablets

PRINCIPAL DISPLAY PANEL – Carton Label

NDC 82576-080-90

REZDIFFRA

(resmetirom) tablets

80 mg

Rx Only

90 Tablets

PRINCIPAL DISPLAY PANEL – Bottle Label

NDC 82576-100-30

REZDIFFRA

(resmetirom) tablets

100 mg

Rx Only

30 Tablets

PRINCIPAL DISPLAY PANEL – Carton Label

NDC 82576-100-30

REZDIFFRA

(resmetirom) tablets

100 mg

Rx Only

30 Tablets

PRINCIPAL DISPLAY PANEL – Bottle Label

NDC 82576-100-90

REZDIFFRA

(resmetirom) tablets

100 mg

Rx Only

90 Tablets

PRINCIPAL DISPLAY PANEL – Carton Label

NDC 82576-100-90

REZDIFFRA

(resmetirom) tablets

100 mg

Rx Only

90 Tablets